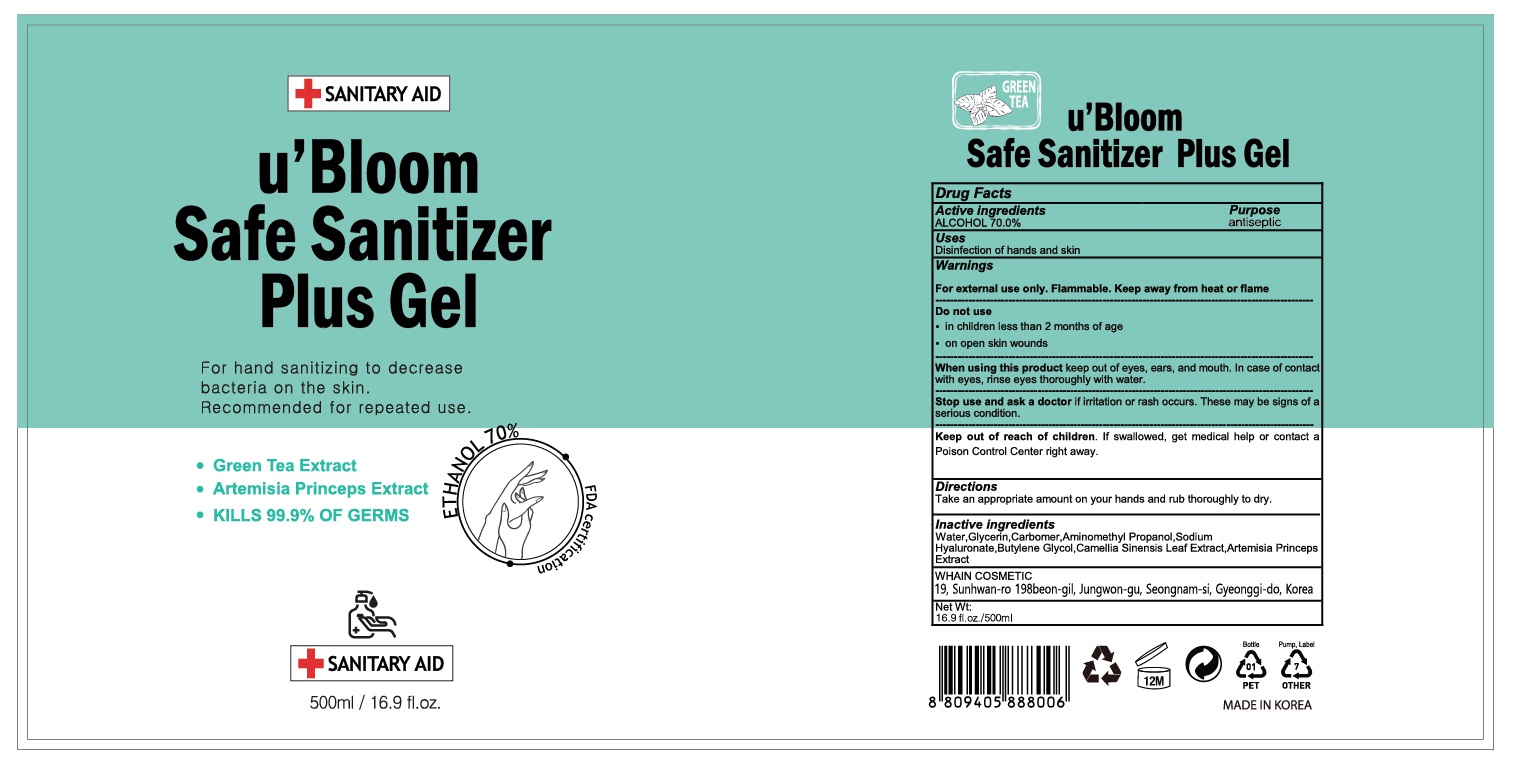 DRUG LABEL: uBloom Safe Sanitizer Plus Gel
NDC: 73823-577 | Form: GEL
Manufacturer: WHAIN COSMETIC
Category: otc | Type: HUMAN OTC DRUG LABEL
Date: 20200517

ACTIVE INGREDIENTS: ALCOHOL 350 mL/500 mL
INACTIVE INGREDIENTS: AMINOMETHYL PROPANEDIOL; GLYCERIN; HYALURONATE SODIUM; BUTYLENE GLYCOL; CARBOMER HOMOPOLYMER, UNSPECIFIED TYPE; WATER; ARTEMISIA PRINCEPS LEAF; GREEN TEA LEAF

[WHAIN COSMETIC] u'Bloom Safe Sanitizer PLus Gel 500 ml : 73823-577